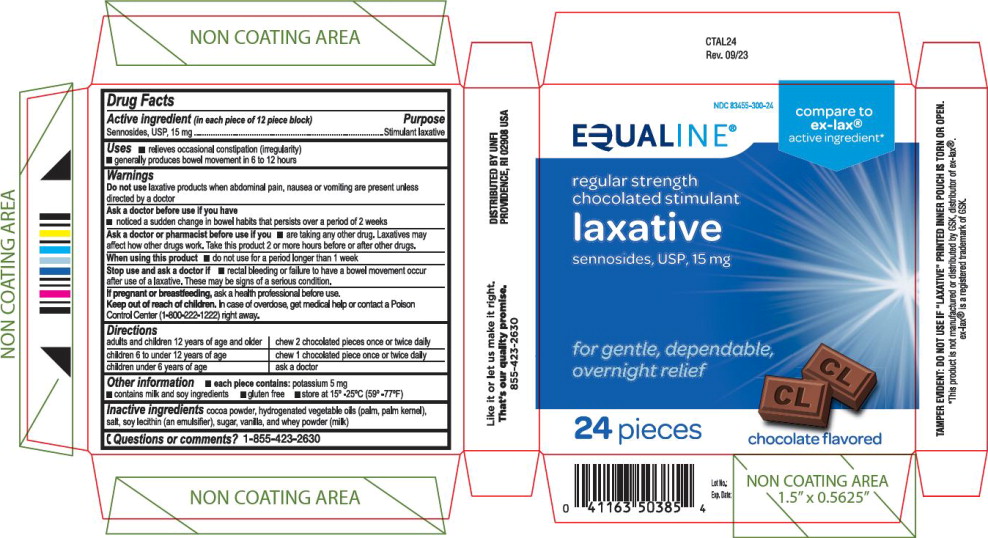 DRUG LABEL: Equaline Regular Strength Chocolated Stimulant Laxative
NDC: 83455-300 | Form: TABLET, CHEWABLE
Manufacturer: United Natural Foods, Inc. dba UNFI
Category: otc | Type: HUMAN OTC DRUG LABEL
Date: 20241226

ACTIVE INGREDIENTS: Sennosides 15 mg/1 1
INACTIVE INGREDIENTS: cocoa; palm kernel oil; sodium chloride; lecithin, soybean; sucrose; vanilla; whey

Drug Facts

Active ingredient (in each piece of 12 piece block)

Sennosides, USP, 15 mg

Purpose

Stimulant laxative

Uses

- relieves occasional constipation (irregularity)
- generally produces bowel movement in 6 to 12 hours

Warnings

Do not use laxative products when abdominal pain, nausea or vomiting are present unless directed by a doctor

Ask a doctor before use if you have

- noticed a sudden change in bowel habits that persists over a period of 2 weeks

Ask a doctor or pharmacist before use if you

- are taking any other drug. Laxatives may affect how other drugs work. Take this product 2 or more hours before or after other drugs.

When using this product

- do not use for a period longer than 1 week

Stop use and ask a doctor if

- rectal bleeding or failure to have a bowel movement occur after use of a laxative. These may be signs of a serious condition.

PREGNANCY OR BREAST FEEDING

If pregnant or breastfeeding, ask a health professional before use.

Keep out of reach of children. In case of overdose, get medical help or contact a Poison Control Center (1-800-222-1222) right away.

Directions

adults and children 12 years of age and older | chew 2 chocolated pieces once or twice daily
children 6 to under 12 years of age | chew 1 chocolated piece once or twice daily
children under 6 years of age | ask a doctor

Other information

- each piece contains: potassium 5 mg
- contains milk and soy ingredients
- gluten free
- store at 15°-25°C (59°-77°F)

Inactive ingredients

cocoa powder, hydrogenated vegetable oils (palm, palm kernel), salt, soy lecithin (an emulsifier), sugar, vanilla, and whey powder (milk)

Questions or comments?

1-855-423-2630

Principal Display Panel – 15 mg Carton Label

NDC 83455-300-24

EQUALINE®

compare to
ex-lax®
active ingredient*

regular strength
chocolated stimulant
laxative

sennosides, USP, 15 mg

for gentle, dependable,
overnight relief

24 pieces

chocolate flavored